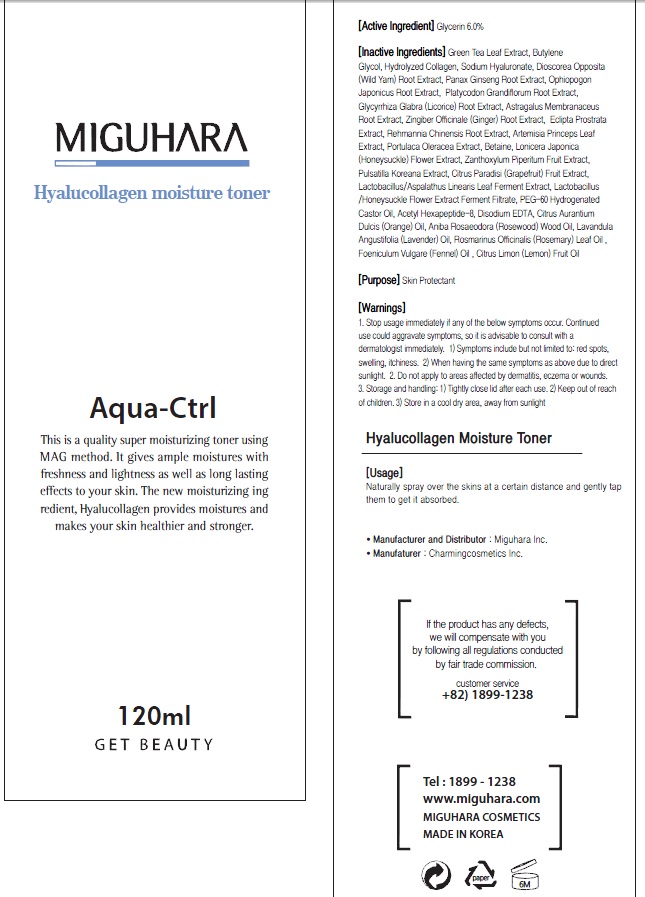 DRUG LABEL: Hyalucollagen Moisture Toner
NDC: 70380-230 | Form: SPRAY
Manufacturer: MIGUHARA
Category: otc | Type: HUMAN OTC DRUG LABEL
Date: 20160222

ACTIVE INGREDIENTS: Glycerin 7.2 g/120 mL
INACTIVE INGREDIENTS: Green Tea Leaf; Butylene Glycol

ACTIVE INGREDIENT

Active Ingredient: Glycerin 6.0%

INACTIVE INGREDIENT

Inactive Ingredients: Green Tea Leaf Extract, Butylene Glycol, Hydrolyzed Collagen, Sodium Hyaluronate, Dioscorea Opposita (Wild Yam) Root Extract, Panax Ginseng Root Extract, Ophiopogon Japonicus Root Extract, Platycodon Grandiflorum Root Extract, Glycyrrhiza Glabra (Licorice) Root Extract, Astragalus Membranaceus Root Extract, Zingiber Officinale (Ginger) Root Extract, Eclipta Prostrata Extract, Rehmannia Chinensis Root Extract, Artemisia Princeps Leaf Extract, Portulaca Oleracea Extract, Betaine, Lonicera Japonica (Honeysuckle) Flower Extract, Zanthoxylum Piperitum Fruit Extract, Pulsatilla Koreana Extract, Citrus Paradisi (Grapefruit) Fruit Extract, Lactobacillus/Aspalathus Linearis Leaf Ferment Extract, Lactobacillus/Honeysuckle Flower Extract Ferment Filtrate, PEG-60 Hydrogenated Castor Oil, Acetyl Hexapeptide-8, Disodium EDTA, Citrus Aurantium Dulcis (Orange) Oil, Aniba Rosaeodora (Rosewood) Wood Oil, Lavandula Angustifolia (Lavender) Oil, Rosmarinus Officinalis (Rosemary) Leaf Oil , Foeniculum Vulgare (Fennel) Oil , Citrus Limon (Lemon) Fruit Oi

PURPOSE

Purpose: Skin Protectant

WARNINGS

1. Stop usage immediately if any of the below symptoms occur. Continued use could aggravate symptoms, so it is advisable to consult with a dermatologist immediately. 1) Symptoms include but not limited to: red spots, swelling, itchiness. 2) When having the same symptoms as above due to direct sunlight. 2. Do not apply to areas affected by dermatitis, eczema or wounds. 3. Storage and handling: 1) Tightly close lid after each use. 2 Keep out of reach of children 3) Store in a cool dry area, away from sunlight

KEEP OUT OF REACH OF CHILDREN

Usage

Usage: Naturally spray over the skins at a certain distance and gently tap them to get it absorbed.

Usage

Usage: Naturally spray over the skins at a certain distance and gently tap them to get it absorbed.